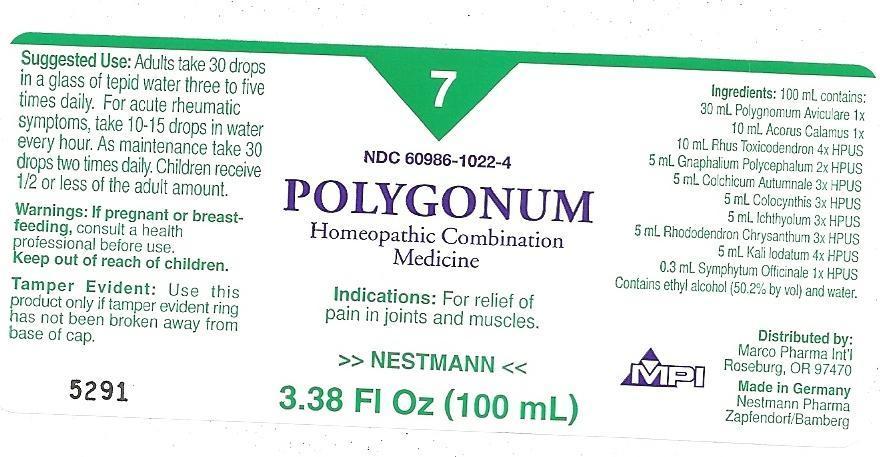 DRUG LABEL: Polygonum
NDC: 60986-1022 | Form: LIQUID
Manufacturer: Marco Pharma International LLC.
Category: homeopathic | Type: HUMAN OTC DRUG LABEL
Date: 20111123

ACTIVE INGREDIENTS: POLYGONUM AVICULARE TOP 1 [hp_X]/100 mL; ACORUS CALAMUS WHOLE 1 [hp_X]/100 mL; TOXICODENDRON PUBESCENS LEAF 4 [hp_X]/100 mL; PSEUDOGNAPHALIUM OBTUSIFOLIUM 2 [hp_X]/100 mL; RHODODENDRON AUREUM LEAF 3 [hp_X]/100 mL; CITRULLUS COLOCYNTHIS FRUIT PULP 3 [hp_X]/100 mL; COLCHICUM AUTUMNALE BULB 3 [hp_X]/100 mL; POTASSIUM IODIDE 4 [hp_X]/100 mL; ICHTHAMMOL 3 [hp_X]/100 mL; COMFREY ROOT 1 [hp_X]/100 mL
INACTIVE INGREDIENTS: ALCOHOL; WATER

Drug Facts

Active Ingredients

Polygonum Aviculare 1x

Acorus Calamus 1x

Rhus Toxicodendron 4xHPUS

Gnaphalium Polycephalum 2xHPUS

Rhododendron Chrysanthum 3xHPUS

Colocynthis 3xHPUS

Colchicum Autumnale 3xHPUS

Kali Iodatum 4xHPUS

Ichthyolum 3xHPUS

Symphytum Officinale 1XHPUS

The letters HPUS indicates that the components in this product are officially monographed in the Homeopathic Pharmacopoeia of United Sates.

Purpose

Relief of pain in joints and muscles.

Keep out of reach of children.

Suggested use

Adults: take 30 drops in a glass of tepid water three to five times daily. For acute rheumatic symptoms, take 10 - 15 drops in waterevery hour. As maintenance take 30 drops two times daily. Children receive 1/2 or less of the adult amount.

Warnings

If pregnant or breast-feeding, consult a health professional before use.

DOSAGE AND ADMINISTRATION

(Read Suggested Use Section)

Inactive Ingredients

Ethyl Alcohol (50.2% by vol.) and Water

PACKAGE LABEL

MM1